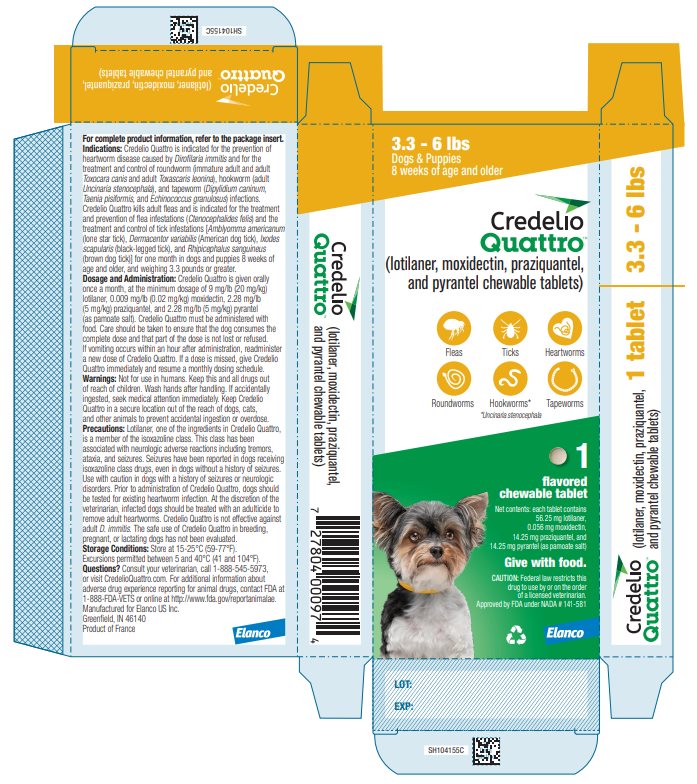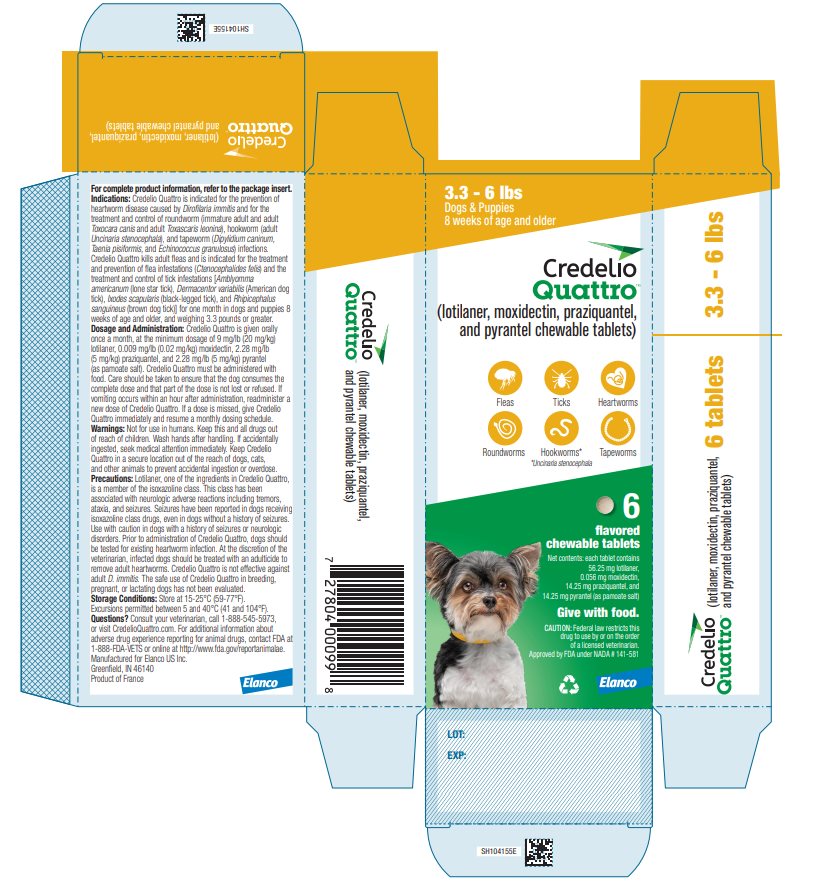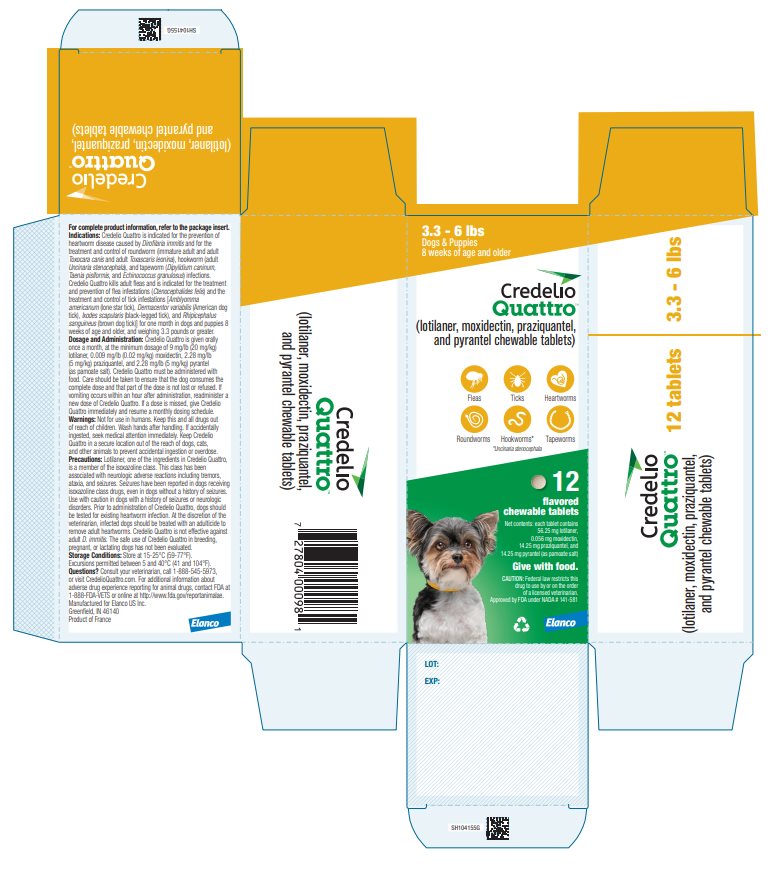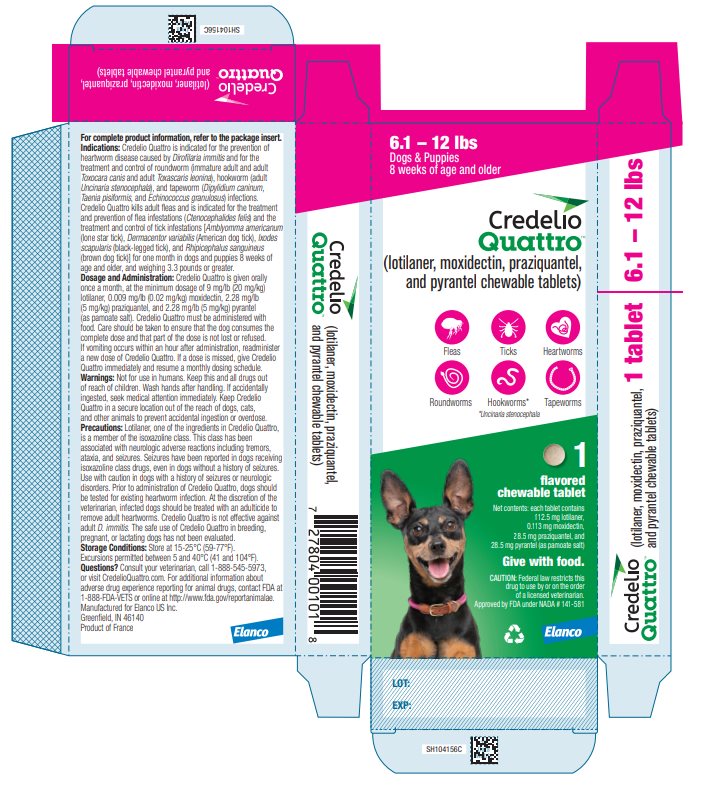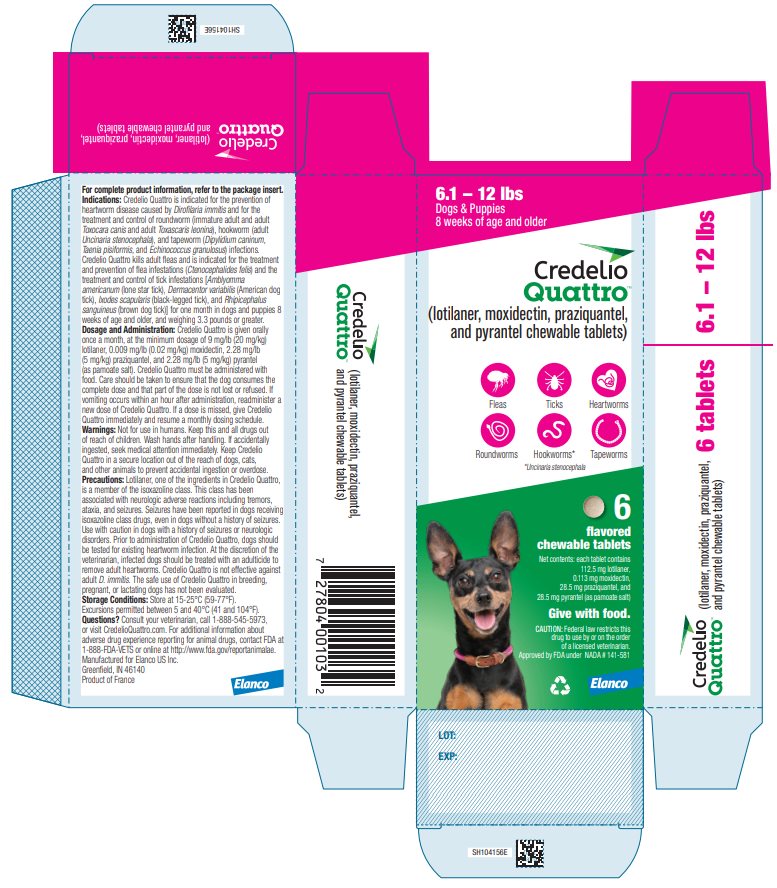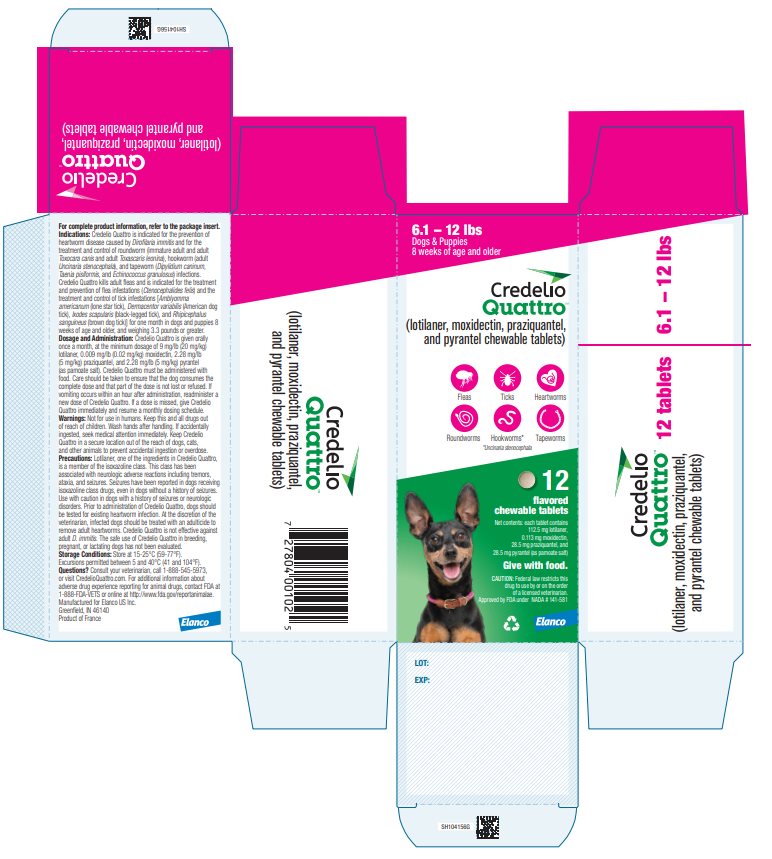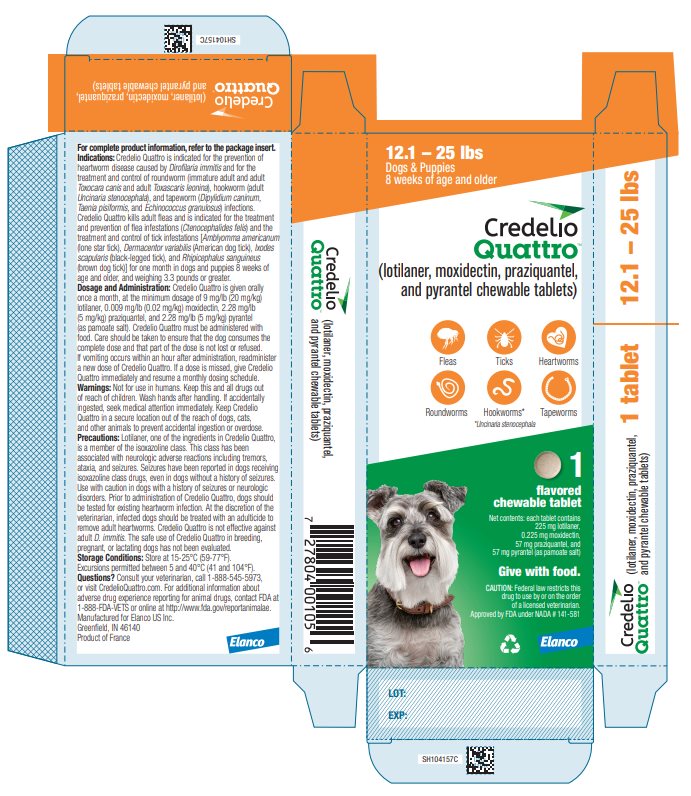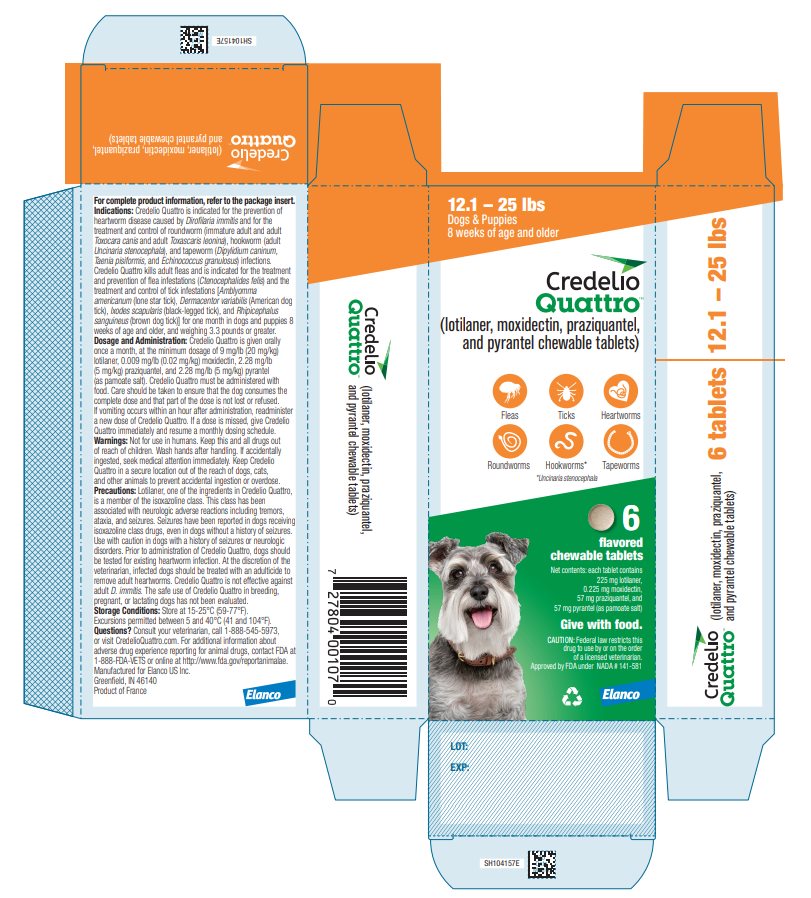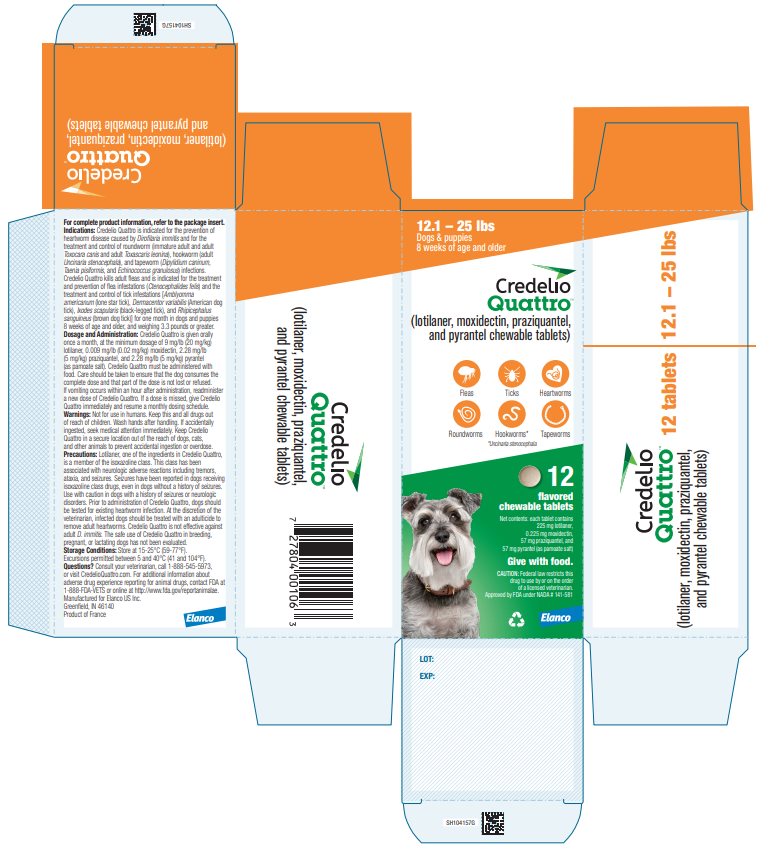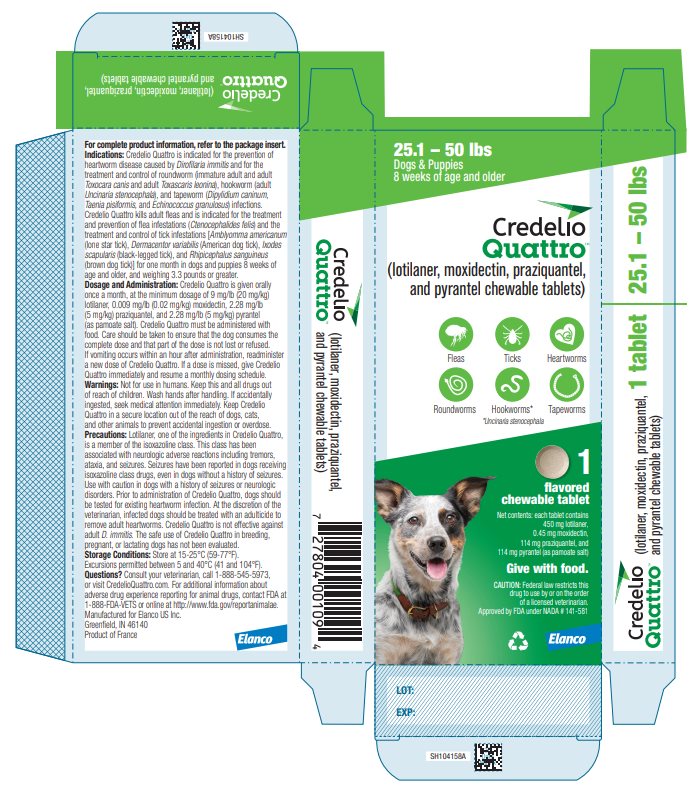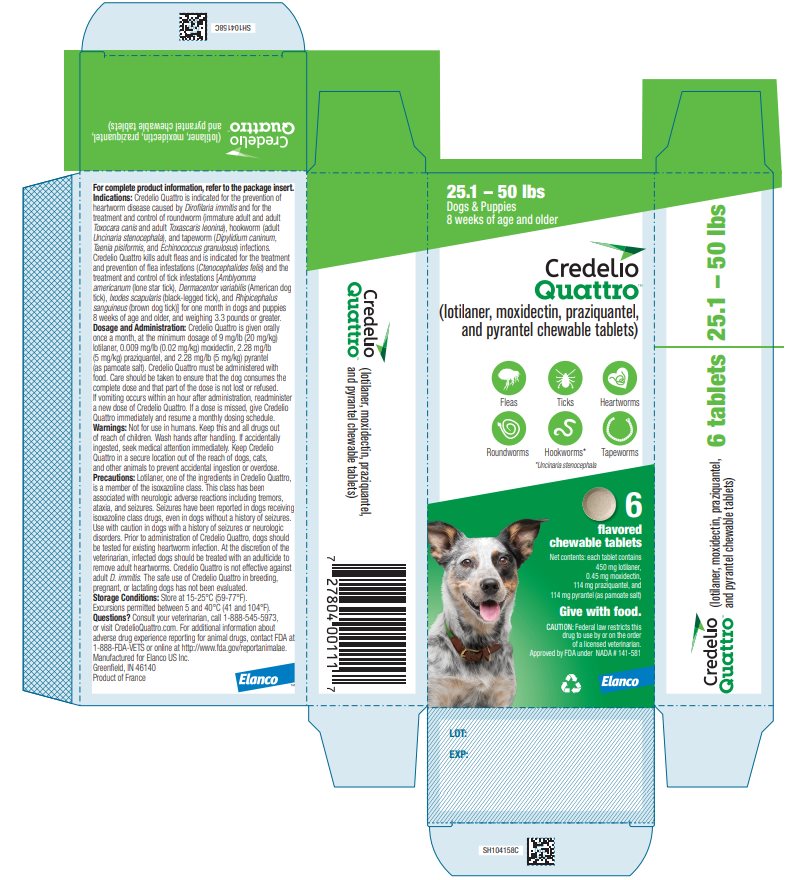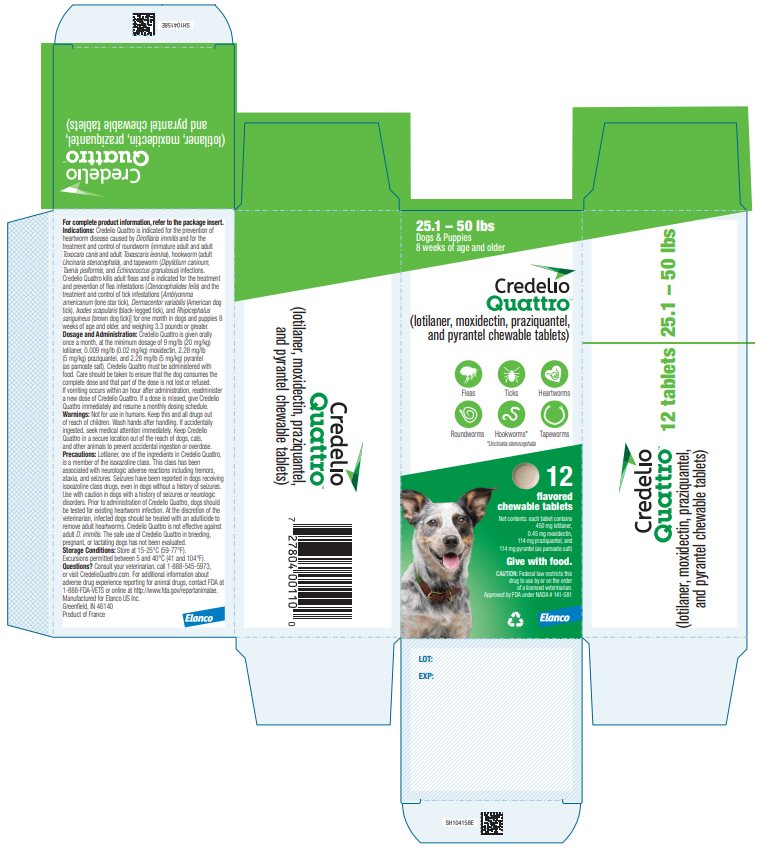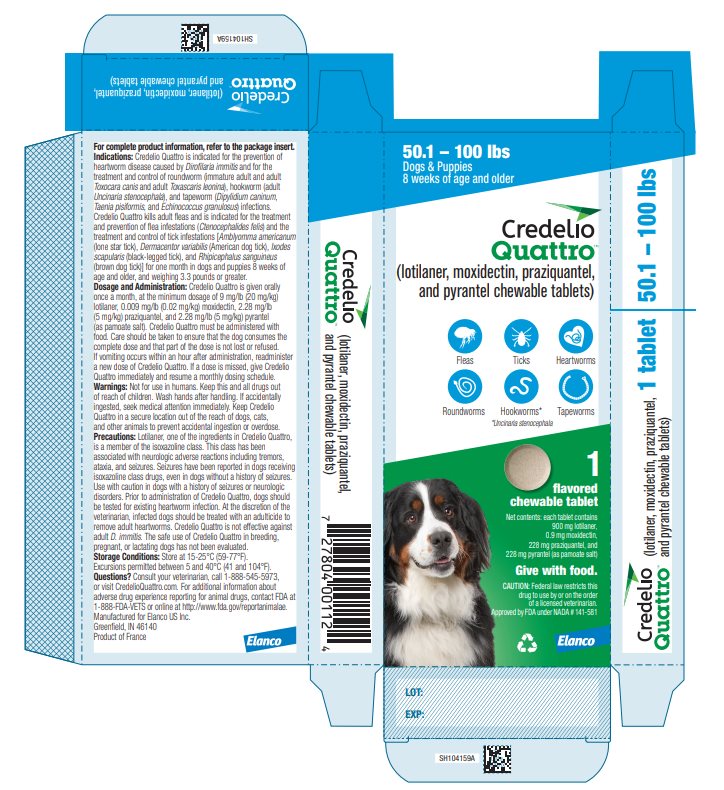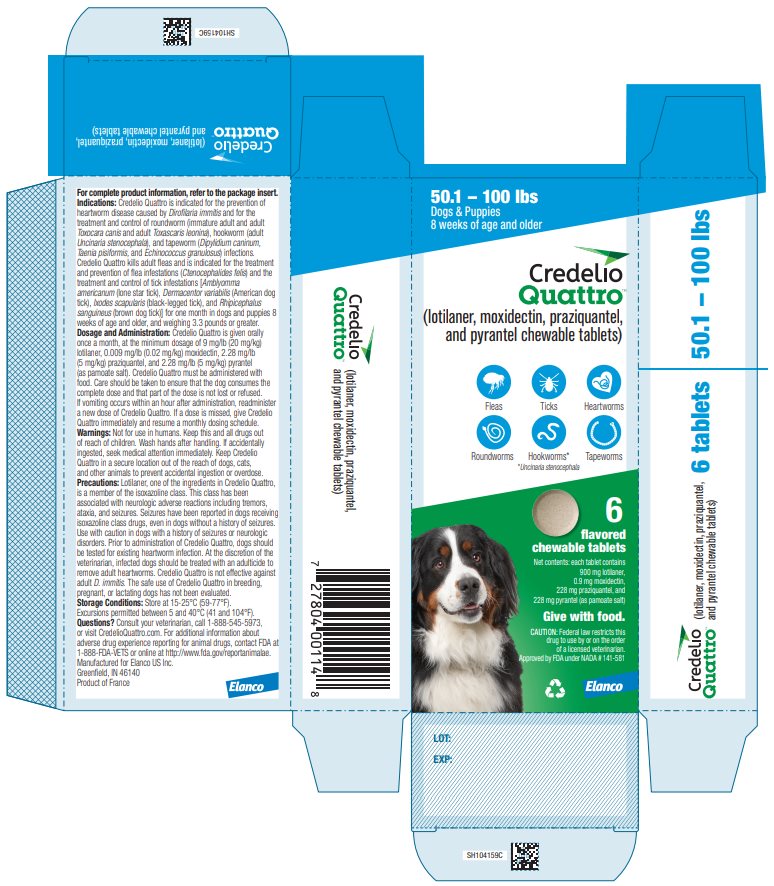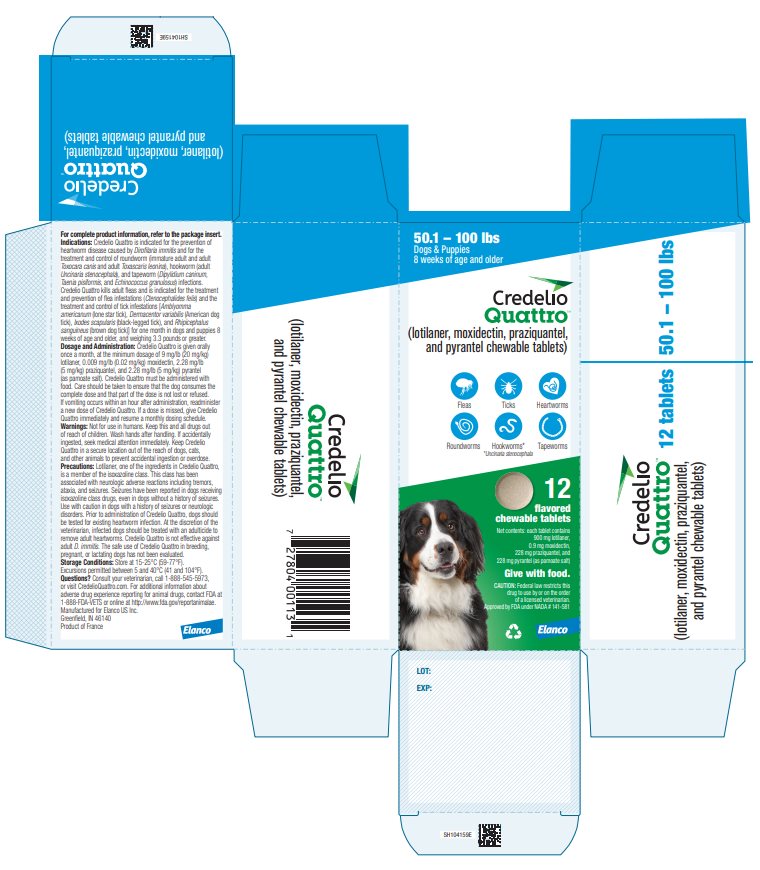 DRUG LABEL: Credelio Quattro
NDC: 58198-5825 | Form: TABLET
Manufacturer: Elanco US Inc.
Category: animal | Type: PRESCRIPTION ANIMAL DRUG LABEL
Date: 20241021

ACTIVE INGREDIENTS: LOTILANER 56.5 mg/1 1; MOXIDECTIN 0.056 mg/1 1; PRAZIQUANTEL 14.25 mg/1 1; PYRANTEL PAMOATE 14.25 mg/1 1

Credelio
Quattro™
(lotilaner, moxidectin, praziquantel, and pyrantel chewable tablets)

Flavored Chewable Tablets

For oral use in dogs only

CAUTION

Federal law restricts this drug to use by or on the order of a licensed veterinarian.

DESCRIPTION

Credelio Quattro (lotilaner, moxidectin, praziquantel, and pyrantel chewable tablets) are flavored chewable tablets available in five sizes for oral administration to dogs and puppies according to their weight. Each chewable is formulated to provide minimum doses of 9 mg/lb (20 mg/kg) lotilaner, 0.009 mg/lb (0.02 mg/kg) moxidectin, 2.28 mg/lb (5 mg/kg) praziquantel, and 2.28 mg/lb (5 mg/kg) pyrantel (as pamoate salt).

Lotilaner is a member of the isoxazoline class of parasiticides and the chemical name is 5-[(5S)-4,5-dihydro-5-(3,4,5-trichlorophenyl)-5-(trifluoromethyl)-3-isoxazolyl]-3-methyl-N-[2-oxo-2-[(2,2,2-trifluoroethyl)amino]ethyl]- 2-thiophenecarboxamide.

Moxidectin is a semisynthetic macrocyclic lactone derived from the actinomycete Streptomycetes cyaneogriseus noncyanogenus. The chemical name for moxidectin is [6R,23E,25S(E)]-5-O- demethyl-28-deoxy-25-(1,3-dimethyl-1-butenyl)- 6,28-epoxy-23-(methoxyimino) milbemycin B.

Praziquantel is an isoquinolone anthelmintic with the chemical name 2-(cyclohexylcarbonyl)-1,2,3,6,7,-11b-hexahydro-4H-pyrazino [2,1- a]isoquinolin-4-one.

Pyrantel is a member of the tetrahydropyrimidine family of compounds. Its chemical name is (E)- 1,4,5,6-tetrahydro-1-methyl-2-[2-(2-thienyl) vinyl] pyrimidine 4, 4’ methylenebis [3-hydroxy-2-naphthoate](1:1).

INDICATIONS

Credelio Quattro is indicated for the prevention of heartworm disease caused by Dirofilaria immitis and for the treatment and control of roundworm (immature adult and adult Toxocara canis and adult Toxascaris leonina), hookworm (adult Uncinaria stenocephala), and tapeworm (Dipylidium caninum, Taenia pisiformis, and Echinococcus granulosus) infections. Credelio Quattro kills adult fleas and is indicated for the treatment and prevention of flea infestations (Ctenocephalides felis) and the treatment and control of tick infestations [Amblyomma americanum (lone star tick), Dermacentor variabilis (American dog tick), Ixodes scapularis (black-legged tick), and Rhipicephalus sanguineus (brown dog tick)] for one month in dogs and puppies 8 weeks of age and older, and weighing 3.3 pounds or greater.

DOSAGE AND ADMINISTRATION

Credelio Quattro is given orally once a month, at the minimum dosage of 9 mg/lb (20 mg/kg) lotilaner, 0.009 mg/lb (0.02 mg/kg) moxidectin, 2.28 mg/lb (5 mg/kg) praziquantel, and 2.28 mg/lb (5 mg/kg) pyrantel (as pamoate salt). Credelio Quattro must be administered with food (see Clinical Pharmacology). Care should be taken to ensure that the dog consumes the complete dose and that part of the dose is not lost or refused. If vomiting occurs within an hour after administration, readminister a new dose of Credelio Quattro. If a dose is missed, give Credelio Quattro immediately and resume a monthly dosing schedule.

Dosing Schedule:

Body Weight (lbs) | Tablets to Administer | Lotilaner per Tablet (mg) | Moxidectin per Tablet (mg) | Praziquantel per Tablet (mg) | Pyrantel* per Tablet (mg)
3.3 – 6 | 1 | 56.25 | 0.056 | 14.25 | 14.25
6.1 – 12 | 1 | 112.5 | 0.113 | 28.5 | 28.5
12.1 – 25 | 1 | 225 | 0.225 | 57 | 57
25.1 – 50 | 1 | 450 | 0.45 | 114 | 114
50.1 – 100 | 1 | 900 | 0.9 | 228 | 228
> 100 | Administer the appropriate combination of tablets
*As pamoate salt

Heartworm Prevention

Credelio Quattro should be administered year-round at monthly intervals or at least within 1 month of the animal’s first seasonal exposure to mosquitoes and continuing until at least 1 month after the dog’s last seasonal exposure. If a dose is missed, give Credelio Quattro immediately and resume monthly dosing. When replacing a monthly heartworm preventive product, Credelio Quattro should be given within 1 month of the last dose of the former medication.

Intestinal Nematode and Cestode Treatment and Control

Credelio Quattro should be administered as a single dose for the treatment of roundworm, hookworm, and tapeworm infections. Monthly use of Credelio Quattro will control any subsequent infections. Dogs may be exposed to and can become infected with gastrointestinal worms throughout the year, regardless of season or climate. Clients should be advised of appropriate measures to prevent reinfection of their dog with intestinal parasites.

Flea Treatment and Prevention

Treatment with Credelio Quattro should be administered year-round at monthly intervals or started at least 1 month before fleas become active. To minimize the likelihood of flea re-infestation, it is important to treat all dogs and cats within a household with a flea control product.

Tick Treatment and Control

Treatment with Credelio Quattro can begin at any time of the year. Credelio Quattro should be administered year-round at monthly intervals or started at least 1 month before ticks become active.

CONTRAINDICATIONS

There are no known contraindications for the use of Credelio Quattro.

WARNINGS

Not for use in humans. Keep this and all drugs out of reach of children. Wash hands after handling. If accidentally ingested, seek medical attention immediately.

Keep Credelio Quattro in a secure location out of reach of dogs, cats, and other animals to prevent accidental ingestion or overdose.

PRECAUTIONS

Lotilaner, one of the ingredients in Credelio Quattro, is a member of the isoxazoline class. This class has been associated with neurologic adverse reactions including tremors, ataxia, and seizures. Seizures have been reported in dogs receiving isoxazoline class drugs, even in dogs without a history of seizures. Use with caution in dogs with a history of seizures or neurologic disorders.

Prior to administration of Credelio Quattro, dogs should be tested for existing heartworm infections. At the discretion of the veterinarian, infected dogs should be treated with an adulticide to remove adult heartworms. Credelio Quattro is not effective against adult D. immitis.

The safe use of Credelio Quattro in breeding, pregnant, or lactating dogs has not been evaluated.

ADVERSE REACTIONS

In a field safety and effectiveness study, Credelio Quattro was administered to dogs for the prevention of heartworm disease. The study included a total of 372 dogs treated once monthly for up to 11 treatments (191 treated with Credelio Quattro and 181 treated with an active control). Over the 330-day study period, all observations of potential adverse reactions were recorded.

Adverse reactions seen during the field study are summarized in the table below.

Dogs with Adverse Reactions in the Field Study

Clinical Sign | Credelio Quattro N=191 Number (Percentage) | Active Control N=181 Number (Percentage)
Diarrhea, with or without blood* | 21 (11%) | 15 (8.3%)
Vomiting | 18 (9.4%) | 8 (4.4%)
Lethargy | 12 (6.3%) | 1 (0.6%)
Anorexia | 11 (5.8%) | 5 (2.8%)
Dermatitis | 10 (5.2%) | 8 (4.4%)
Weight Loss | 6 (3.1%) | 3 (1.7%)
Pruritus (itching) | 3 (1.6%) | 1 (0.6%)
Alopecia (hair loss) | 2 (1.0%) | 4 (2.2%)
Seizure | 1 (0.5%) | 4 (2.2%)
Ataxia | 1 (0.5%) | 1 (0.6%)
Nystagmus | 1 (0.5%) | 0 (0.0%)
Anisocoria | 1 (0.5%) | 1 (0.6%)
*Four dogs administered Credelio Quattro and five dogs administered the active control had bloody diarrhea.

One geriatric dog receiving Credelio Quattro experienced two episodes of vomiting, ataxia, and nystagmus, 11 days apart, with the first episode occurring two days after the eighth dose. The dog recovered within 24 hours after the first episode and 1 hour after the second episode and completed the study. One dog receiving Credelio Quattro was observed by the investigator to have anisocoria during scheduled physical examinations one month after the ninth dose and one month after the eleventh dose.

In a U.S. field study, 165 dogs received a combination of lotilaner, moxidectin, and praziquantel, three of the active ingredients at the same doses as in Credelio Quattro, monthly for up to 11 months. Two dogs with no history of seizures experienced seizures during the study. One of the dogs developed cluster seizures and was removed from the study. Ataxia was also observed in one other dog three days after the first dose.

In a U.S. field study, one dog administered lotilaner alone, a component of Credelio Quattro, was observed with intermittent head tremors within 1.5 hours of administration of vaccines, an ear cleaning performed by the owner, and its first dose of lotilaner. The head tremors resolved within 24 hours without treatment. The owner elected to withdraw the dog from the study.

In an Australian field study, one dog with a history of seizures experienced seizure activity (tremors and glazed eyes) six days after receiving lotilaner alone. The dog recovered without treatment and completed the study. In a U.S. field study, two dogs with a history of seizures received lotilaner alone and experienced no seizures throughout the study.

CONTACT INFORMATION

For a copy of the Safety Data Sheet (SDS) or to report suspected adverse drug events, contact Elanco US Inc. at 1-888-545-5973.

For additional information about adverse drug experience reporting for animal drugs, contact FDA at 1-888-FDA-VETS or http://www.fda.gov/reportanimalae.

INFORMATION FOR ANIMAL OWNER

Echinococcus granulosus is a tapeworm found in wild canids and domestic dogs. E. granulosus can infect humans and cause serious disease (hydatid disease). Owners of dogs living in areas where E. granulosus is endemic should be instructed on how to minimize their risk of exposure to this parasite, as well as their dog’s risk of exposure. Although Credelio Quattro was 100% effective in laboratory studies in dogs against E. granulosus, no studies have been conducted to show that the use of this product will decrease the incidence of hydatid disease in humans.

CLINICAL PHARMACOLOGY

Mechanism of Action

Credelio Quattro contains four active pharmaceutical ingredients, lotilaner, moxidectin, praziquantel, and pyrantel (as pamoate salt).

Lotilaner is an ectoparasiticide belonging to the isoxazoline group. Lotilaner inhibits insect and acarine gamma-aminobutyric acid (GABA)-gated chloride channels. This inhibition blocks the transfer of chloride ions across cell membranes, which results in uncontrolled neuromuscular activity leading to death of insects and acarines. The selective toxicity of lotilaner between insects and acarines and mammals may be inferred by the differential sensitivity of the insects and acarines’ GABA receptors versus mammalian GABA receptors.

Moxidectin is an endectocide in the macrocyclic lactone class. Moxidectin acts by interfering with the chloride channel-mediated neurotransmission in the parasite. This results in paralysis and death of the parasite.

Praziquantel’s mode of action is not precisely known, but treated tapeworms undergo muscular paralysis accompanied by a rapid influx of calcium ions and the disruption of the tegument.

Pyrantel is a nematocide belonging to the tetrahydropyrimidine class. Pyrantel acts as a depolarizing, neuromuscular-blocking agent in susceptible parasites, causing paralysis and death or expulsion of the parasite.

Pharmacokinetics

Due to reduced drug bioavailability of lotilaner in the fasted state, Credelio Quattro must be administered with a meal or within 30 minutes after feeding.

Following a single oral administration of Credelio Quattro at the minimum labeled dose in the fed state or a single intravenous administration of 5 mg lotilaner, 0.005 mg moxidectin, 1.25 mg praziquantel, and 1.25 mg pyrantel per kg body weight to Beagle dogs (1.5 to 2.5 years old), the mean oral bioavailability for lotilaner, praziquantel, and pyrantel was 93%, 41%, and 31%, respectively. Bioavailability for moxidectin is not reported due to insufficient data to adequately describe the elimination phase following intravenous administration. For Credelio Quattro, the area under the curve from time of dosing to the time of the last measurable concentration (AUClast) was 5970, 1.75, 1.54, and 0.857 mg*h/L for lotilaner, moxidectin, praziquantel, and pyrantel, respectively. Peak concentrations (Cmax) of 9070, 15.3, 390, and 122 ng/mL were reached (Tmax) 10, 4.5, 0.75, and 2.5 h after dosing for lotilaner, moxidectin, praziquantel, and pyrantel, respectively. Mean plasma elimination half‐lives were 806, 634, 3.64, and 4.87 h for lotilaner, moxidectin, praziquantel, and pyrantel, respectively.

Following nine oral administrations of Credelio Quattro at 1X, 3X, and 5X the maximum labeled dose of 40 mg/kg lotilaner, 0.04 mg/kg moxidectin, 10 mg/kg praziquantel, and 10 mg/kg pyrantel, every 28 days in 8-week-old Beagle dogs, moxidectin and lotilaner area under the curve from time of dosing to the time of the last measurable concentration (AUClast) increased approximately in a less than proportional manner, whereas praziquantel AUClast increased approximately in a more than proportional manner from 1X to 5X after most study doses. Pyrantel AUClast increased approximately in a proportional manner from 1X to 5X observed after first, sixth, and last doses. Within the 1X group, accumulation was observed between Days 0 and 224 with geometric mean accumulation ratios for AUClast of 6.2 and 7.9 for lotilaner and moxidectin, respectively. Concentrations of praziquantel and pyrantel prior to each dose were below the limit of quantification.

EFFECTIVENESS

Heartworm Prevention

In two well-controlled laboratory studies, a single oral dose of Credelio Quattro was 100% effective in preventing the development of adult D. immitis in dogs inoculated with infective larvae 30 days before administration.

In a well-controlled U.S. field study consisting of 156 dogs administered Credelio Quattro and 149 administered an active control for 11 consecutive months, no dogs treated with Credelio Quattro tested positive for heartworm disease. All dogs treated with Credelio Quattro were negative for D. immitis antigen and blood microfilariae at study completion on Day 330.

Intestinal Nematode and Cestode Treatment and Control

In well-controlled laboratory studies, a single dose of Credelio Quattro was ≥ 97.0% effective against immature adult and adult Toxocara canis, adult Toxascaris leonina, and adult Uncinaria stenocephala infections.

In well‐controlled laboratory studies, a single dose of Credelio Quattro was 100% effective against Echinococcus granulosus. In separate well-controlled laboratory studies, praziquantel alone was 100% effective against Echinococcus granulosus, Dipylidium caninum, and Taenia pisiformis.

Flea Treatment and Prevention

In a well-controlled laboratory study, Credelio Quattro was 100% effective against adult fleas 24 hours after administration or infestation for 36 days. In a separate laboratory study, lotilaner alone began to kill fleas 4 hours after administration or infestation, with greater than 99% of fleas killed within 8 hours after administration or infestation for 35 days.

In a well-controlled U.S. field study conducted in households with existing flea infestations of varying severity, flea reductions of 99.5% to 100% were observed over the course of three monthly treatments with lotilaner alone. Dogs with signs of flea allergy dermatitis showed improvement in erythema, papules, scaling, alopecia, dermatitis/pyodermatitis, and pruritus as a direct result of eliminating fleas.

Tick Treatment and Control

In well-controlled laboratory studies, Credelio Quattro was ≥ 97.1% effective against Rhipicephalus sanguineus ticks 48 hours after administration or infestation for 32 days. In well-controlled laboratory studies, lotilaner alone was > 97% effective against Amblyomma americanum, Dermacentor variabilis, Ixodes scapularis, and Rhipicephalus sanguineus ticks 48 hours after administration or infestation for 30 days. In a well-controlled European laboratory study, lotilaner alone started killing Ixodes ricinus ticks within 4 hours after administration.

Palatability: In the U.S. field study, which included 552 doses administered to 191 dogs, dogs voluntarily consumed 59.8% of Credelio Quattro doses from an empty bowl, on the floor, or when offered by hand, and an additional 28.4% of doses when offered with food. The administration of 11.8% of doses required placement of the chewable tablet in the back of the dog’s mouth. All doses were administered within 30 minutes of a meal.

TARGET ANIMAL SAFETY

Margin of Safety

Credelio Quattro was administered orally at 0X, 1X, 3X, and 5X the maximum labeled doses at 28-day intervals for nine treatments to 32 healthy, 8-week-old Beagle puppies. Dogs in the control group received placebo. Credelio Quattro-related clinical chemistry findings included increased bile acids in two of the 3X dogs. Minimal mononuclear cell infiltration of the liver was noted microscopically in five control dogs, two 1X dogs, three 3X dogs, and five 5X dogs. One control dog, one 1X dog, two 3X dogs, and none of the 5X dogs also had minimal extramedullary hematopoiesis. Credelio Quattro-related clinical observations included a dose-dependent increase in discolored feces, diarrhea, and vomiting. All dogs recovered without treatment. Hypersalivation associated with vomiting on the day of dosing occurred in two of the 5X dogs.

Avermectin Sensitive Collie Safety

Credelio Quattro was administered orally at 0X, 1X, 2X, and 5X the maximum labeled dose at 28-day intervals for three treatments to 32 healthy, avermectin sensitive Collie dogs. Dogs in the control group received a vehicle control. One dog in each of the control, 2X, and 5X groups had transient mild depression. Salivation and vomiting was observed in a dose-dependent manner in the 1X, 2X, and 5X groups. Diarrhea, with or without blood, was observed in all groups, including controls, and resolved without treatment.

Heartworm Positive Safety

Credelio Quattro was administered orally at 0X, 1X, and 3X the maximum labeled dose at 28-day intervals for three treatments to 24 healthy, Beagle dogs with patent adult heartworm infections and circulating microfilariae. Dogs in the control group received placebo. Diarrhea and/or vomiting occurred in all dogs in the 3X group at various times up to 12 hours post-dose. Diarrhea occurred in fewer dogs in the 1X and control groups. All dogs experiencing post-dose gastrointestinal issues recovered without treatment. Hypersensitivity reactions (e.g., anaphylaxis, shock, collapse, respiratory distress, or depression) were not observed in any dog.

Field Safety

In a well-controlled field study, Credelio Quattro was used concurrently with other medications such as vaccines, antimicrobials, anthelmintics, antiemetics, steroidal and nonsteroidal anti-inflammatory drugs (NSAIDs), anesthetics, and analgesics. No adverse reactions were associated with the concurrent use of Credelio Quattro and other medications.

HOW SUPPLIED

Credelio Quattro (lotilaner, moxidectin, praziquantel, and pyrantel chewable tablets) is available in five strengths of flavored chewable tablets formulated according to the weight of the dog (see Dosage and Administration). Each chewable tablet size is available in packages of 1, 6, or 12 tablets.

STORAGE INFORMATION

Store at 15-25°C (59-77°F). Excursions permitted between 5 and 40°C (41 and 104°F).

Approved by FDA under NADA # 141-581

Manufactured for: Elanco US Inc, Greenfield, IN 46140

Credelio Quattro, Elanco and the diagonal bar logo are trademarks of Elanco or its affiliates.
© 2024 Elanco or its affiliates

June 2024

ElancoTM

Principal Display Panel

3.3 - 6 lbs
Dogs & Puppies
8 weeks of age and older

Credelio
Quattro™
(lotilaner, moxidectin, praziquantel,
and pyrantel chewable tablets)

Fleas Ticks Heartworms
Roundworms Hookworms* Tapeworms
* Uncinaria stenocephala

1
flavored
chewable tablet

Net contents: each tablet contains
56.25 mg lotilaner,
0.056 mg moxidectin,
14.25 mg praziquantel, and
14.25 mg pyrantel (as pamoate salt)

Give with food.

CAUTION: Federal law restricts this
drug to use by or on the order
of a licensed veterinarian.
Approved by FDA under NADA # 141-581

Elanco

3.3 - 6 lbs
Dogs & Puppies
8 weeks of age and older

Credelio
Quattro™
(lotilaner, moxidectin, praziquantel,
and pyrantel chewable tablets)

Fleas Ticks Heartworms
Roundworms Hookworms* Tapeworms
* Uncinaria stenocephala

6
flavored
chewable tablets

Net contents: each tablet contains
56.25 mg lotilaner,
0.056 mg moxidectin,
14.25 mg praziquantel, and
14.25 mg pyrantel (as pamoate salt)

Give with food.

CAUTION: Federal law restricts this
drug to use by or on the order
of a licensed veterinarian.
Approved by FDA under NADA # 141-581

Elanco

3.3 - 6 lbs
Dogs & Puppies
8 weeks of age and older

Credelio
Quattro™
(lotilaner, moxidectin, praziquantel,
and pyrantel chewable tablets)

Fleas Ticks Heartworms
Roundworms Hookworms* Tapeworms
* Uncinaria stenocephala

12
flavored
chewable tablets

Net contents: each tablet contains
56.25 mg lotilaner,
0.056 mg moxidectin,
14.25 mg praziquantel, and
14.25 mg pyrantel (as pamoate salt)

Give with food.

CAUTION: Federal law restricts this
drug to use by or on the order
of a licensed veterinarian.
Approved by FDA under NADA # 141-581

Elanco

Principal Display Panel

6.1 – 12 lbs
Dogs & Puppies
8 weeks of age and older

Credelio
Quattro™
(lotilaner, moxidectin, praziquantel,
and pyrantel chewable tablets)

Fleas Ticks Heartworms
Roundworms Hookworms* Tapeworms
* Uncinaria stenocephala

1
flavored
chewable tablet

Net contents: each tablet contains
112.5 mg lotilaner,
0.113 mg moxidectin,
28.5 mg praziquantel, and
28.5 mg pyrantel (as pamoate salt)

Give with food.

CAUTION: Federal law restricts this
drug to use by or on the order
of a licensed veterinarian.
Approved by FDA under NADA # 141-581

Elanco

6.1 – 12 lbs
Dogs & Puppies
8 weeks of age and older

Credelio
Quattro™
(lotilaner, moxidectin, praziquantel,
and pyrantel chewable tablets)

Fleas Ticks Heartworms
Roundworms Hookworms* Tapeworms
* Uncinaria stenocephala

6
flavored
chewable tablets

Net contents: each tablet contains
112.5 mg lotilaner,
0.113 mg moxidectin,
28.5 mg praziquantel, and
28.5 mg pyrantel (as pamoate salt)

Give with food.

CAUTION: Federal law restricts this
drug to use by or on the order
of a licensed veterinarian.
Approved by FDA under NADA # 141-581

Elanco

6.1 – 12 lbs
Dogs & Puppies
8 weeks of age and older

Credelio
Quattro™
(lotilaner, moxidectin, praziquantel,
and pyrantel chewable tablets)

Fleas Ticks Heartworms
Roundworms Hookworms* Tapeworms
* Uncinaria stenocephala

12
flavored
chewable tablets

Net contents: each tablet contains
112.5 mg lotilaner,
0.113 mg moxidectin,
28.5 mg praziquantel, and
28.5 mg pyrantel (as pamoate salt)

Give with food.

CAUTION: Federal law restricts this
drug to use by or on the order
of a licensed veterinarian.
Approved by FDA under NADA # 141-581

Elanco

Principal Display Panel

12.1 – 25 lbs
Dogs & Puppies
8 weeks of age and older

Credelio
Quattro™
(lotilaner, moxidectin, praziquantel,
and pyrantel chewable tablets)

Fleas Ticks Heartworms
Roundworms Hookworms* Tapeworms
* Uncinaria stenocephala

1
flavored
chewable tablet

Net contents: each tablet contains
225 mg lotilaner,
0.225 mg moxidectin,
57 mg praziquantel, and
57 mg pyrantel (as pamoate salt)

Give with food.

CAUTION: Federal law restricts this
drug to use by or on the order
of a licensed veterinarian.
Approved by FDA under NADA # 141-581

Elanco

12.1 – 25 lbs
Dogs & Puppies
8 weeks of age and older

Credelio
Quattro™
(lotilaner, moxidectin, praziquantel,
and pyrantel chewable tablets)

Fleas Ticks Heartworms
Roundworms Hookworms* Tapeworms
* Uncinaria stenocephala

6
flavored
chewable tablets

Net contents: each tablet contains
225 mg lotilaner,
0.225 mg moxidectin,
57 mg praziquantel, and
57 mg pyrantel (as pamoate salt)

Give with food.

CAUTION: Federal law restricts this
drug to use by or on the order
of a licensed veterinarian.
Approved by FDA under NADA # 141-581

Elanco

12.1 – 25 lbs
Dogs & Puppies
8 weeks of age and older

Credelio
Quattro™
(lotilaner, moxidectin, praziquantel,
and pyrantel chewable tablets)

Fleas Ticks Heartworms
Roundworms Hookworms* Tapeworms
* Uncinaria stenocephala

12
flavored
chewable tablets

Net contents: each tablet contains
225 mg lotilaner,
0.225 mg moxidectin,
57 mg praziquantel, and
57 mg pyrantel (as pamoate salt)

Give with food.

CAUTION: Federal law restricts this
drug to use by or on the order
of a licensed veterinarian.
Approved by FDA under NADA # 141-581

Elanco

Principal Display Panel

25.1 – 50 lbs
Dogs & Puppies
8 weeks of age and older

Credelio
Quattro™
(lotilaner, moxidectin, praziquantel,
and pyrantel chewable tablets)

Fleas Ticks Heartworms
Roundworms Hookworms* Tapeworms
* Uncinaria stenocephala

1
flavored
chewable tablet

Net contents: each tablet contains
450 mg lotilaner,
0.45 mg moxidectin,
114 mg praziquantel, and
114 mg pyrantel (as pamoate salt)

Give with food.

CAUTION: Federal law restricts this
drug to use by or on the order
of a licensed veterinarian.
Approved by FDA under NADA # 141-581

Elanco

25.1 – 50 lbs
Dogs & Puppies
8 weeks of age and older

Credelio
Quattro™
(lotilaner, moxidectin, praziquantel,
and pyrantel chewable tablets)

Fleas Ticks Heartworms
Roundworms Hookworms* Tapeworms
* Uncinaria stenocephala

6
flavored
chewable tablets

Net contents: each tablet contains
450 mg lotilaner,
0.45 mg moxidectin,
114 mg praziquantel, and
114 mg pyrantel (as pamoate salt)

Give with food.

CAUTION: Federal law restricts this
drug to use by or on the order
of a licensed veterinarian.
Approved by FDA under NADA # 141-581

Elanco

25.1 – 50 lbs
Dogs & Puppies
8 weeks of age and older

Credelio
Quattro™
(lotilaner, moxidectin, praziquantel,
and pyrantel chewable tablets)

Fleas Ticks Heartworms
Roundworms Hookworms* Tapeworms
* Uncinaria stenocephala

12
flavored
chewable tablets

Net contents: each tablet contains
450 mg lotilaner,
0.45 mg moxidectin,
114 mg praziquantel, and
114 mg pyrantel (as pamoate salt)

Give with food.

CAUTION: Federal law restricts this
drug to use by or on the order
of a licensed veterinarian.
Approved by FDA under NADA # 141-581

Elanco

Principal Display Panel

50.1 – 100 lbs
Dogs & Puppies
8 weeks of age and older

Credelio
Quattro™
(lotilaner, moxidectin, praziquantel,
and pyrantel chewable tablets)

Fleas Ticks Heartworms
Roundworms Hookworms* Tapeworms
* Uncinaria stenocephala

1
flavored
chewable tablet

Net contents: each tablet contains
900 mg lotilaner,
0.9 mg moxidectin,
228 mg praziquantel, and
228 mg pyrantel (as pamoate salt)

Give with food.

CAUTION: Federal law restricts this
drug to use by or on the order
of a licensed veterinarian.
Approved by FDA under NADA # 141-581

Elanco

50.1 – 100 lbs
Dogs & Puppies
8 weeks of age and older

Credelio
Quattro™
(lotilaner, moxidectin, praziquantel,
and pyrantel chewable tablets)

Fleas Ticks Heartworms
Roundworms Hookworms* Tapeworms
* Uncinaria stenocephala

6
flavored
chewable tablets

Net contents: each tablet contains
900 mg lotilaner,
0.9 mg moxidectin,
228 mg praziquantel, and
228 mg pyrantel (as pamoate salt)

Give with food.

CAUTION: Federal law restricts this
drug to use by or on the order
of a licensed veterinarian.
Approved by FDA under NADA # 141-581

Elanco

50.1 – 100 lbs
Dogs & Puppies
8 weeks of age and older

Credelio
Quattro™
(lotilaner, moxidectin, praziquantel,
and pyrantel chewable tablets)

Fleas Ticks Heartworms
Roundworms Hookworms* Tapeworms
* Uncinaria stenocephala

12
flavored
chewable tablets

Net contents: each tablet contains
900 mg lotilaner,
0.9 mg moxidectin,
228 mg praziquantel, and
228 mg pyrantel (as pamoate salt)

Give with food.

CAUTION: Federal law restricts this
drug to use by or on the order
of a licensed veterinarian.
Approved by FDA under NADA # 141-581

Elanco